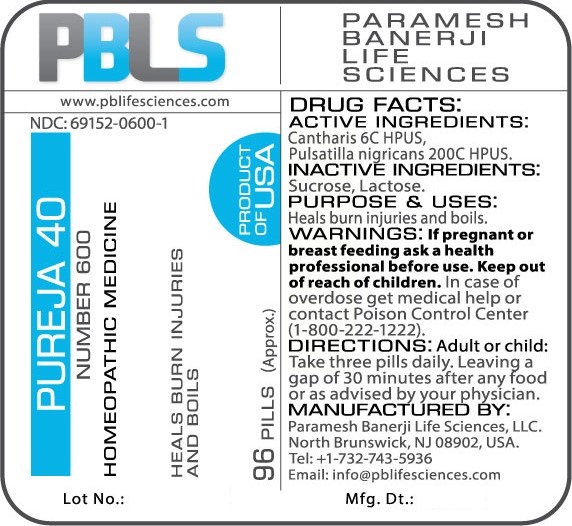 DRUG LABEL: Pureja 40 Number 600
NDC: 69152-0600 | Form: PELLET
Manufacturer: Paramesh Banerji Life Sciences LLC
Category: homeopathic | Type: HUMAN OTC DRUG LABEL
Date: 20170524

ACTIVE INGREDIENTS: PULSATILLA PRATENSIS 200 [hp_C]/1 1; LYTTA VESICATORIA 6 [hp_C]/1 1
INACTIVE INGREDIENTS: SUCROSE; LACTOSE

DRUG FACTS: Active Ingredients

Cantharis 6C HPUS, Pulsatilla nigricans 200C HPUS

Inactive Ingredients

Sucrose, Lactose

Purpose

Heals burn injuries and boils

Uses

Heals burn injuries and boils

Warnings

If pregnant or breast feeding ask a health professional before use.

Keep out of reach of children. In case of overdose, get medical help or contact a Poison Control Center (1-800-222-1222) right away.

Direction

Adult or child: Take three pills daily. Leaving a gap of 30 minutes after any food or as advised by your physician.

Manufactured by

Paramesh Banerji Life Sciences, LLC.

North Brunswick, NJ 08902, USA.

Tel: +1-732-743-5936

Email: info@pblifesciences.com

Principal Display Panel

NDC: 69152-0600-1

Pureja 40

Number 600

Homeopathic Medicine

Heals burn injuries and boils

96 Pills (Approx.)

Product of USA